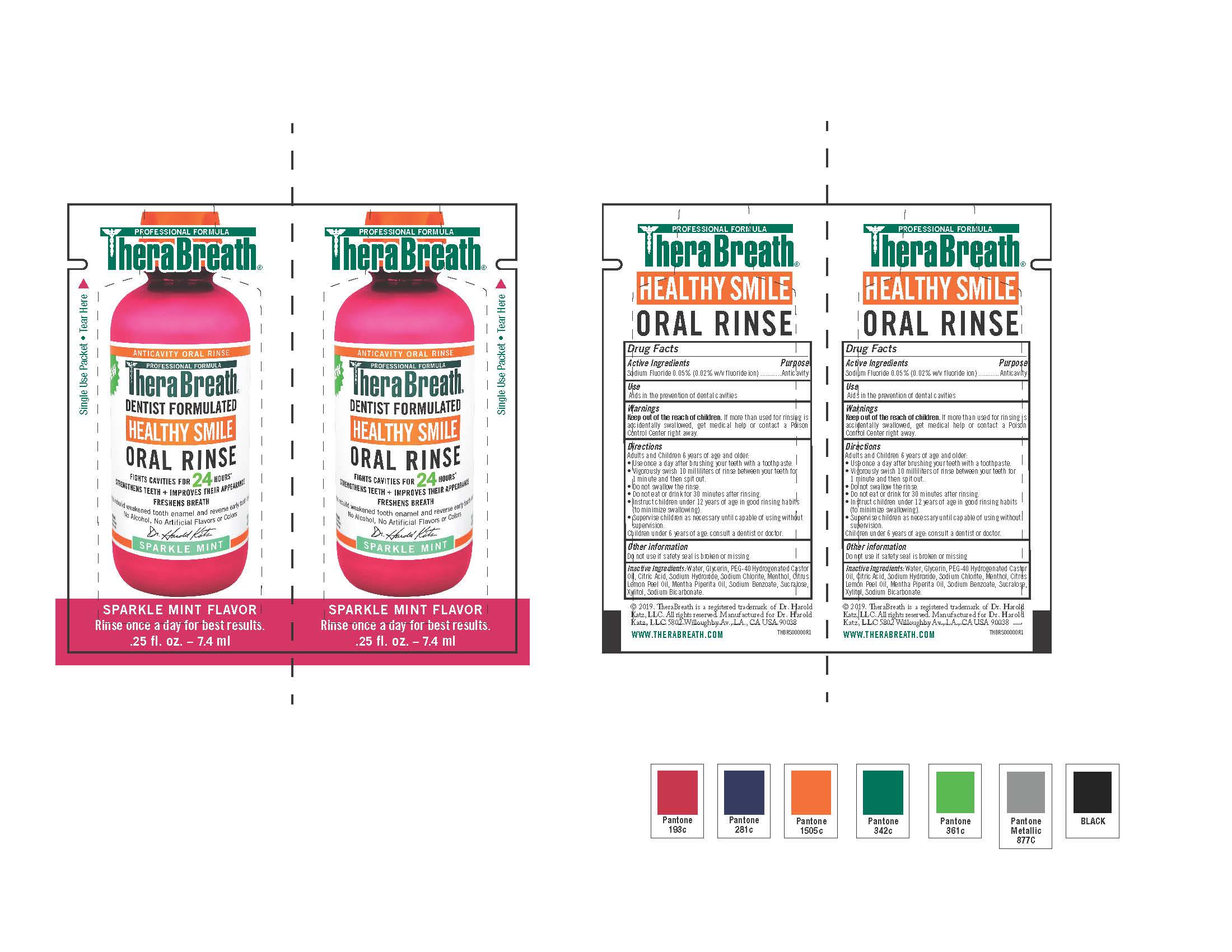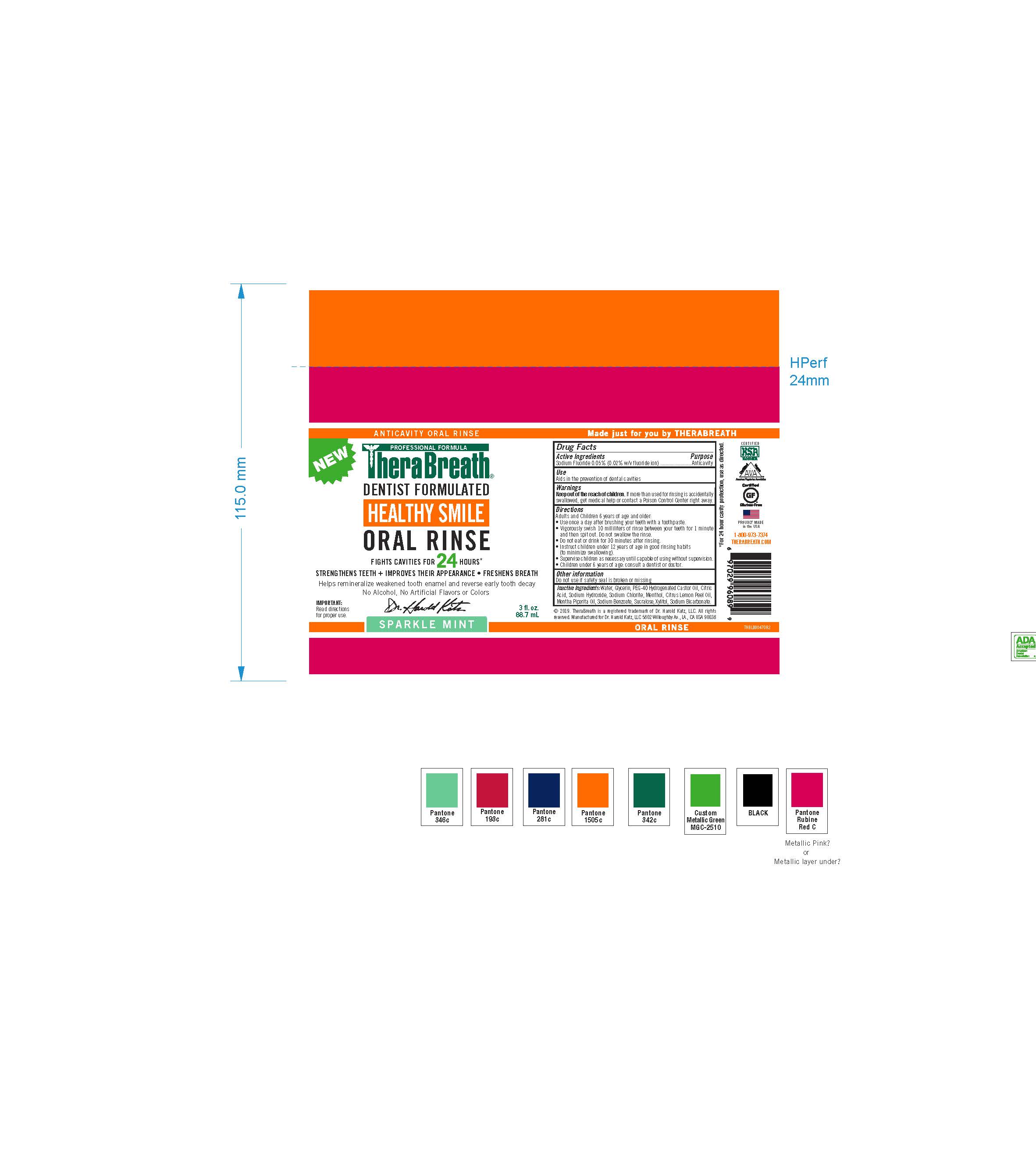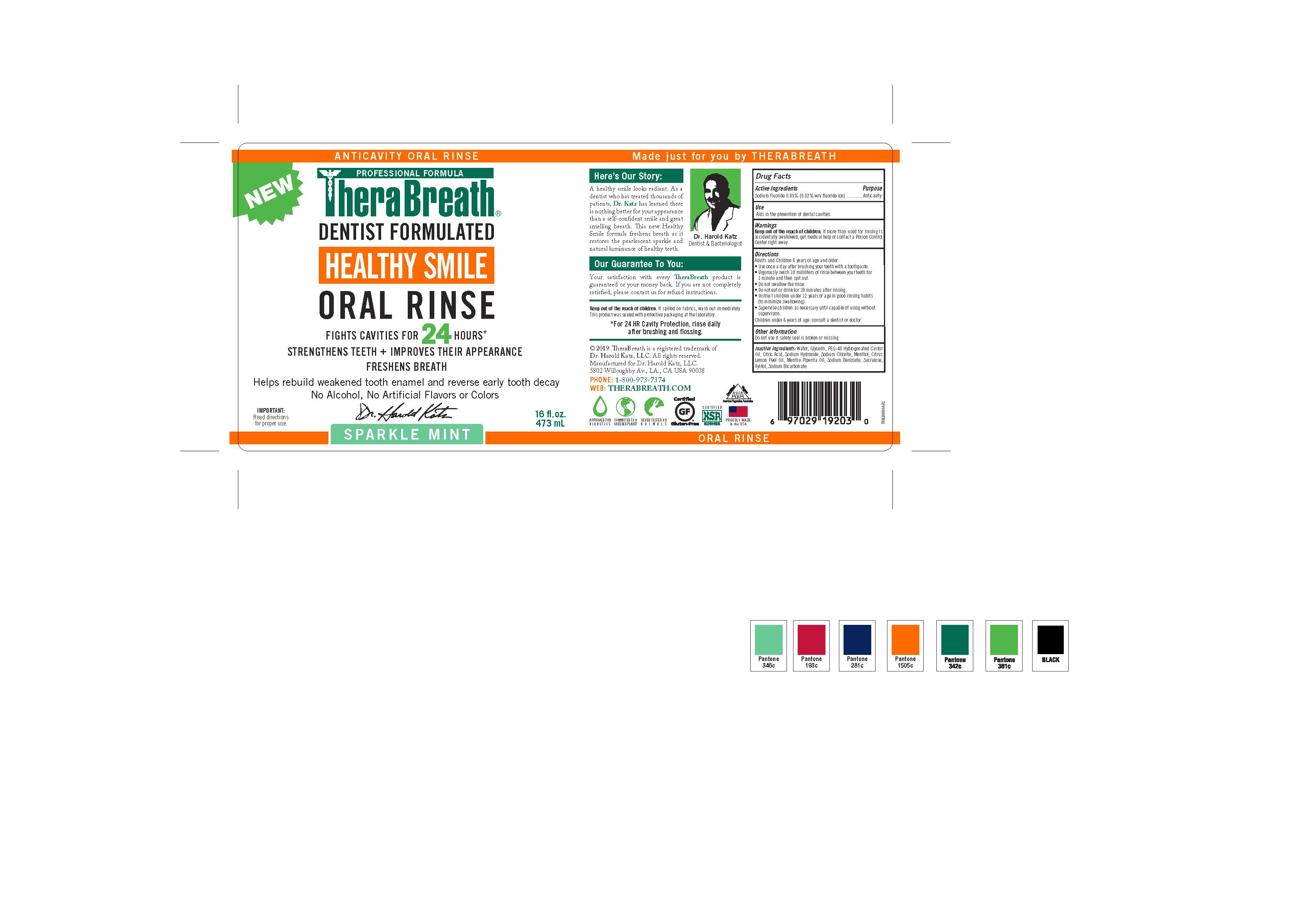 DRUG LABEL: TheraBreath Healthy Smile Oral Rinse
NDC: 72551-246 | Form: RINSE
Manufacturer: Dr. Harold Katz, LLC
Category: otc | Type: HUMAN OTC DRUG LABEL
Date: 20220204

ACTIVE INGREDIENTS: SODIUM FLUORIDE 0.0005 g/1 g
INACTIVE INGREDIENTS: LEMON OIL; SUCRALOSE; WATER; GLYCERIN; XYLITOL; PEG-40 CASTOR OIL; ANHYDROUS CITRIC ACID; SODIUM BICARBONATE; SODIUM HYDROXIDE; MENTHOL; SODIUM CHLORITE; MENTHA PIPERITA; SODIUM BENZOATE

TheraBreath Healthy Smile Oral Rinse

Active Ingredient

Sodium fluoride 0.05% (0.02% w/v fluoride ion)

Purpose

Anticavity

Uses

Aids in the prevention of dental cavities

Warnings

If more than used for brushing is accidentally swallowed, get medical help or contact a Poison Control Center right away.

Directions

Adults and Children 6 years of age and older:

- Use once a day after brushing your teeth with a toothpaste.
- Vigorously swish 10 milliliters of rinse between your teeth for 1 minute and then spit out.
- Do not swallow the rinse.
- Do not eat or drink for 30 minutes after rinsing.
- Instruct children under 12 years of age in good rinsing habits (to minimize swallowing).
- Supervise children as necessary until capable of using without supervision.
- Children under 6 years of age: consult a dentist or doctor.

Other Information

Do not use if safety seal is broken or missing.

Inactive Ingredients

Water, Glycerin, PEG-40 Hydrogenated Castor Oil, Citric Acid, Sodium Hydroxide, Sodium Chlorite, Menthol, Citrus Lemon Peel Oil, Mentha Piperita Oil, Sodium Benzoate, Sucralose, Xylitol, Sodium Bicarbonate.